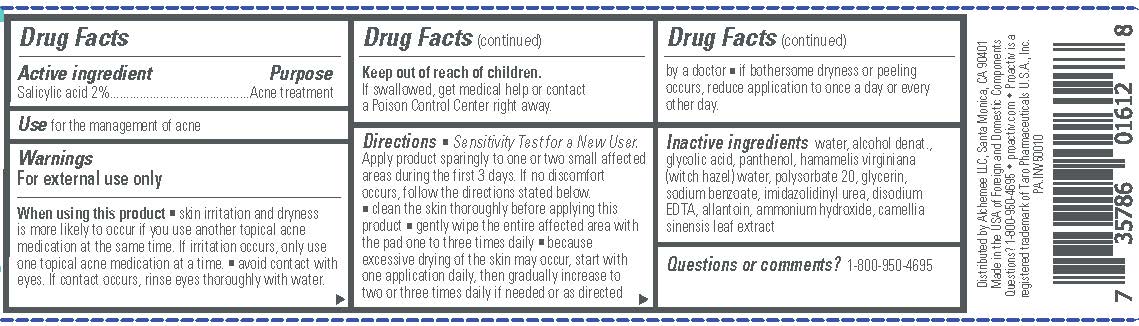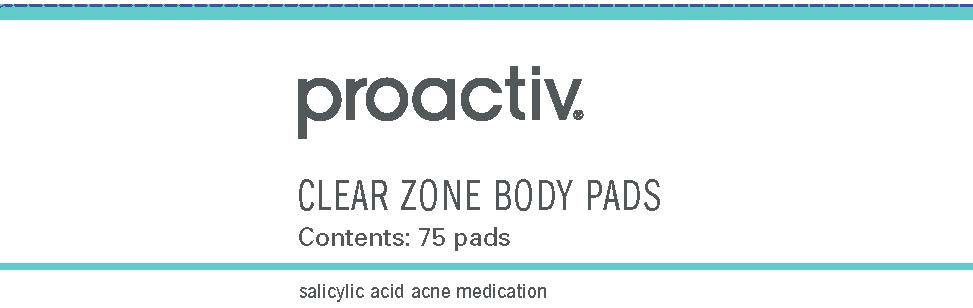 DRUG LABEL: Proactiv CLEAR ZONE BODY PADS
NDC: 11410-056 | Form: LIQUID
Manufacturer: Alchemee, LLC
Category: otc | Type: HUMAN OTC DRUG LABEL
Date: 20260107

ACTIVE INGREDIENTS: SALICYLIC ACID 2 g/100 mL
INACTIVE INGREDIENTS: ALCOHOL; ALLANTOIN; AMMONIA; GREEN TEA LEAF; EDETATE DISODIUM; GLYCERIN; GLYCOLIC ACID; HAMAMELIS VIRGINIANA TOP; IMIDUREA; PANTHENOL; POLYSORBATE 20; SODIUM BENZOATE; WATER

Proactiv®Clear Zone Body Pads

Drug Facts

Active ingredient

Salicylic acid 2%

Purpose

Acne treatment

Use

for the management of acne

Warnings

For external use only When using this product

- skin irritation and dryness is more likely to occur if you use another topical acne medication at the same time. If irritation occurs, only use one topical acne medication at a time.
- avoid contact with eyes. If contact occurs, rinse eyes thoroughly with water.

Keep out of reach of children.

If swallowed, get medical help or contact a Poison Control Center right away.

Directions

- Sensitivity Test for a New User. Apply product sparingly to one or two small affected areas during the first 3 days. If no discomfort occurs, follow the directions stated below.
- clean the skin thoroughly before applying this product
- gently wipe the entire affected area with the pad one to three times daily
- because excessive drying of the skin may occur, start with one application daily, then gradually increase to two or three times daily if needed or as directed by a doctor
- if bothersome dryness or peeling occurs, reduce application to once a day or every other day.

Inactive ingredients

water, alcohol denat., glycolic acid, panthenol, hamamelis virginiana (witch hazel) water, polysorbate 20, glycerin, sodium benzoate, imidazolidinyl urea, disodium EDTA, allantoin, ammonium hydroxide, camellia sinensis leaf extract

Questions or comments?

1-800-950-4695

Distributed by Alchemee LLC, Santa Monica, CA 90401
Made in the USA of Foreign and Domestic Components
Questions? 1-800-950-4695 • proactiv.com • Proactiv is a
registered trademark of Taro Pharmaceuticals U.S.A., Inc.

PRINCIPAL DISPLAY PANEL

proactiv®

CLEAR ZONE BODY PADS

Contents: 75 pads
salicylic acid acne medication